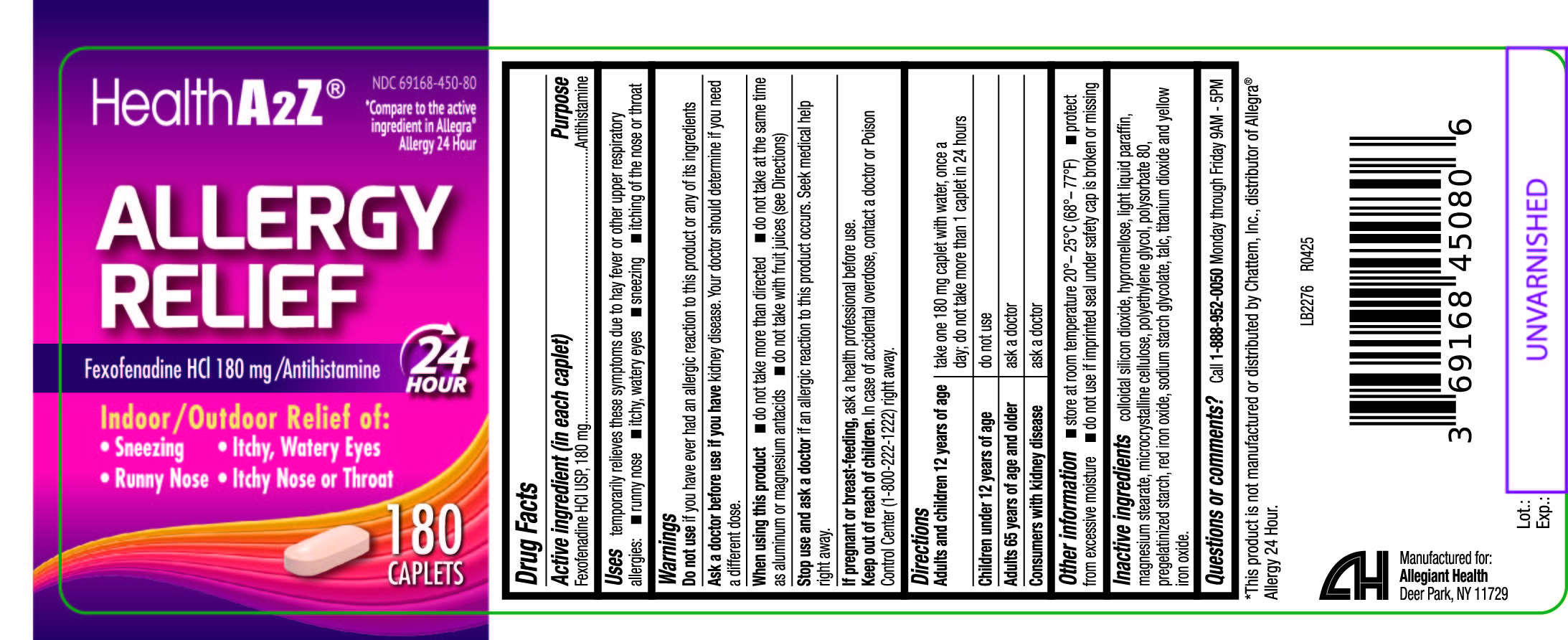 DRUG LABEL: Allergy Relief
NDC: 69168-450 | Form: TABLET
Manufacturer: Allegiant Health
Category: otc | Type: HUMAN OTC DRUG LABEL
Date: 20240417

ACTIVE INGREDIENTS: FEXOFENADINE HYDROCHLORIDE 180 mg/1 1
INACTIVE INGREDIENTS: SILICON DIOXIDE; HYPROMELLOSE, UNSPECIFIED; MAGNESIUM STEARATE; MICROCRYSTALLINE CELLULOSE; POLYETHYLENE GLYCOL, UNSPECIFIED; POLYSORBATE 80; STARCH, CORN; FERRIC OXIDE RED; SODIUM STARCH GLYCOLATE TYPE A POTATO; TALC; TITANIUM DIOXIDE; FERRIC OXIDE YELLOW; LIGHT MINERAL OIL

450 - Allergy Relief

Active ingredient(s)

Fexofenadine hydrochloride USP, 180 mg

Purpose

Antihistamine

Use(s)

temporarily relieves these symptoms due to hay fever or other upper respiratory allergies:

- runny nose
- sneezing
- itchy, watery eyes
- itching of the nose or throat

Warnings

Do not use

if you have ever had an allergic reaction to this product or any of its ingredients.

Ask a doctor before use if

you have kidney disease. Your doctor should determine if you need a different dose.

When using this product

do not take more than directed

- do not take at the same time as aluminum or magnesium antacids
- do not take with fruit juices (see Directions)

Stop use and ask a doctor if

if an allergic reaction to this product occurs. Seek medical help right away.

If pregnant or breastfeeding,

ask a health professional before use.

Keep out of reach of children

In case of accidental overdose, contact a doctor or Poison Control Center (1-800-222-1222) right away.

Directions

Adults and children 12 years of age: take one 180 mg caplet with water, once a and over day; do not take more than 1 caplet in 24 hours

Children under 12 years of age: do not use

Adults 65 years of age and older: ask a doctor

Consumers with kidney disease: ask a doctor

Other information

- store at room temperature 20°– 25°C (68°– 77°F)
- protect from excessive moisture
- do not use if imprinted seal under safety cap is broken or missing

Inactive ingredients

colloidal silicon dioxide, hypromellose, light liquid paraffin, magnesium stearate,
microcrystalline cellulose, polyethylene glycol, polysorbate 80, pregelatinized starch, red
iron oxide, sodium starch glycolate, talc, titanium dioxide and yellow iron oxide.

Questions/Comments

Call 1-888-952-0050 Monday through Friday 9AM - 5PM

Principal Display Panel

Allergy Relief